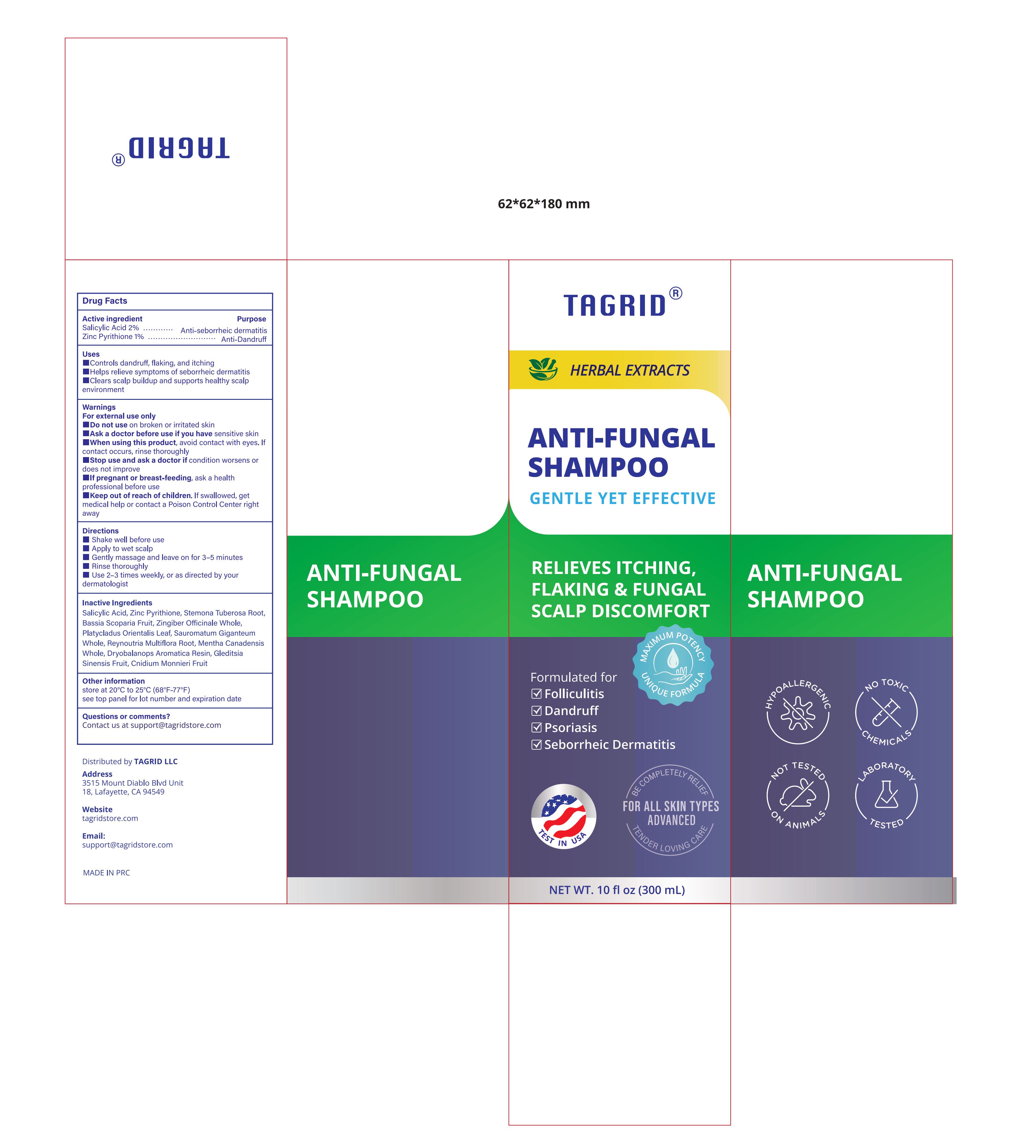 DRUG LABEL: Tagrid ANTI FUNGAL
NDC: 85384-0005 | Form: SHAMPOO
Manufacturer: TAGRID LLC
Category: otc | Type: HUMAN OTC DRUG LABEL
Date: 20250522

ACTIVE INGREDIENTS: SALICYLIC ACID 0.02 g/1 mL; ZINC PYRITHIONE 0.01 g/1 mL
INACTIVE INGREDIENTS: STEMONA TUBEROSA ROOT; BASSIA SCOPARIA FRUIT; CNIDIUM MONNIERI FRUIT; ZINGIBER OFFICINALE WHOLE; PLATYCLADUS ORIENTALIS LEAF; SAUROMATUM GIGANTEUM WHOLE; REYNOUTRIA MULTIFLORA ROOT; MENTHA CANADENSIS WHOLE; DRYOBALANOPS AROMATICA RESIN; GLEDITSIA SINENSIS FRUIT

Active ingredient:

1. Zinc Pyrithione 1%
2. Salicylic Acid 2%

PURPOSE

1. Purpose 1: Anti-Dandruff (Active ingredient：Zinc Pyrithione 1%)
2. Purpose 2: Anti-seborrheic dermatitis (Active ingredient：Salicylic Acid 2%)

Uses:

1. Controls dandruff, flaking, and itching
2. Helps relieve symptoms of seborrheic dermatitis
3. Clears scalp buildup and supports healthy scalp environment

WARNINGS

For external use only

DO NOT USE

On broken or irritated skin.

Ask a doctor before use if you have:
• Sensitive skin

When using this product

• Avoid contact with eyes. If contact occurs, rinse thoroughly.

Stop use and ask a doctor if
• Condition worsens or does not improve

If pregnant or breast-feeding
• Ask a health professional before use

Keep out of reach of children.
If swallowed, get medical help or contact a Poison Control Center right away.

Directions:

1. Shake well before use
2. Apply to wet scalp
3. Gently massage and leave on for 3-5 minutes
4. Rinse thoroughly
5. Use 2-3 times weekly, or as directed by your dermatologist

Other information:

1. store at 20°C to 25°C (68°F-77°F)
2. see top panel for lot number and expiration date

Inactive ingredients:

- Salicylic Acid
- Zinc Pyrithione
- Stemona Tuberosa Root
- Bassia Scoparia Fruit
- Zingiber Officinale Whole
- Platycladus Orientalis Leaf
- Sauromatum Giganteum Whole
- Reynoutria Multiflora Root
- Mentha Canadensis Whole
- Dryobalanops Aromatica Resin
- Gleditsia Sinensis Fruit
- Cnidium Monnieri Fruit

Questions or comments?
Contact us at support@tagridstore.com